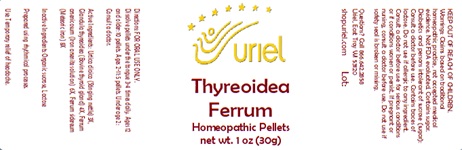 DRUG LABEL: Thyreoidea Ferrum
NDC: 48951-9379 | Form: PELLET
Manufacturer: Uriel Pharmacy Inc.
Category: homeopathic | Type: HUMAN OTC DRUG LABEL
Date: 20240903

ACTIVE INGREDIENTS: THYROID, UNSPECIFIED 4 [hp_X]/1 1; FUCUS VESICULOSUS 3 [hp_X]/1 1; URTICA DIOICA 3 [hp_X]/1 1; FERROUS ARSENATE 6 [hp_X]/1 1; IRON 6 [hp_X]/1 1
INACTIVE INGREDIENTS: SUCROSE; LACTOSE, UNSPECIFIED FORM

Thyreoidea Ferrum

INDICATIONS AND USAGE

Directions: FOR ORAL USE ONLY.

DOSAGE AND ADMINISTRATION

Dissolve pellets under the tongue 3-4 times daily. Ages 12 and older: 10 pellets. Ages 2-11: 5 pellets. Under age 2: Consult a doctor.

ACTIVE INGREDIENT

Active Ingredients: Fucus ves. (Bladderweed) 3X, Glandula thyreoidea (Bovine thyroid gland) 4X, Urtica dioica (Stinging nettle) 3X, Ferrum arsenicosum (Iron arsenite solution) 6X, Ferrum sidereum (Meteoric iron) 6X

Inactive Ingredients: Organic sucrose, Lactose

Prepared using rhythmical processes.

PURPOSE

Use: Temporary relief of headache.

KEEP OUT OF REACH OF CHILDREN.

WARNINGS

Warnings: Claims based on traditional homeopathic practice, not accepted medical evidence. Not FDA evaluated. Contains sugar. Diabetics and persons intolerant of sucrose (sugar): Consult a doctor before use. Contains traces of lactose. Do not use if allergic to any ingredient. Consult a doctor before use for serious conditions or if conditions worsen or persist. If pregnant or nursing, consult a doctor before use. Do not use if safety seal is broken or missing.

Questions? Call 866.642.2858
Uriel, East Troy, WI 53120
shopuriel.com Lot: